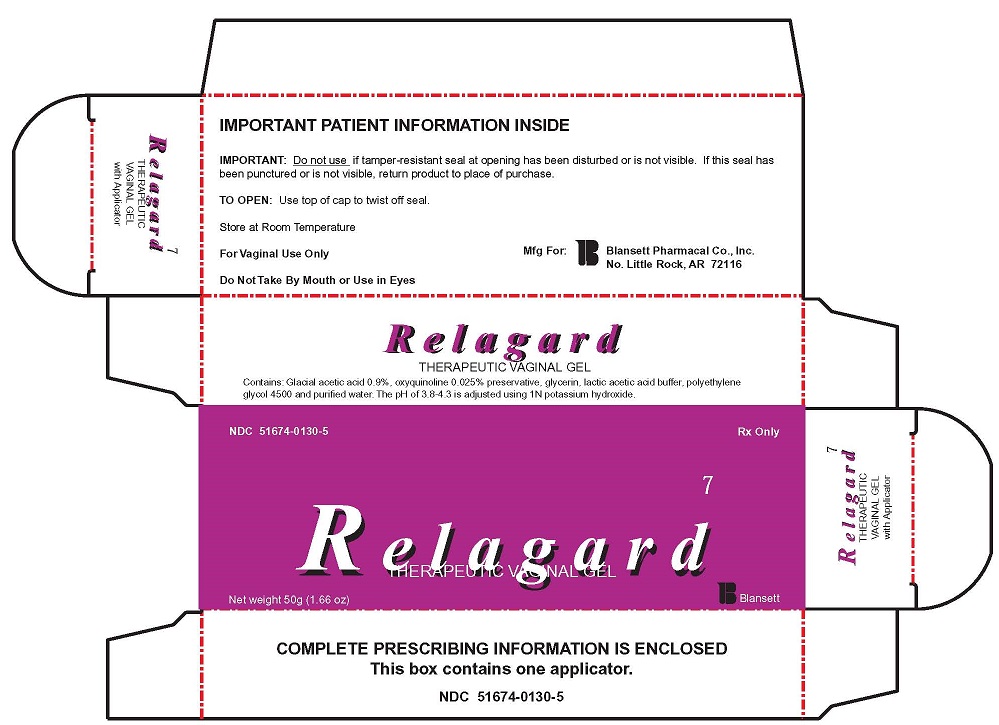 DRUG LABEL: RELEGARD
NDC: 51674-0130 | Form: GEL
Manufacturer: BLANSETT PHARMACAL CO
Category: prescription | Type: HUMAN PRESCRIPTION DRUG LABEL
Date: 20170320

ACTIVE INGREDIENTS: ACETIC ACID 0.9 mg/1 mL; OXYQUINOLINE 0.025 mg/1 mL
INACTIVE INGREDIENTS: GLYCERIN; LACTIC ACID; POLYETHYLENE GLYCOL 4500; WATER; POTASSIUM HYDROXIDE

RELEGARD THERAPEUTIC VAGINAL GEL WITH APPLICATOR

DOSAGE AND ADMINISTRATION

TO OPEN: USE TOP OF CAP TO TWIST OFF SEAL.

FOR VAGINAL USE ONLY.

CONTAINS: GLACIAL ACETIC ACID 0.9%, OXYQUINOLINE 0.025%, PRESERVATIVE, GLYCERIN, LACTIC ACID BUFFER, POLYETHYLENE GLYCOL 4500 AND PURIFIED WATER. THE PH OF 3.8 - 4.3 IS ADJUSTED USING 1N POTASSIUM HYDROXIDE.

DO NOT USE IF TAMPER-RESISTANT SEAL AT OPENING HAS BEEN DISTURBED OR IS NOT VISIBLE. IF THIS SEAL HAS BEEN PUNCTURED OR IS NOT VISIBLE, RETURN PRODUCT TO PLACE OF PURCHASE.

STORE AT ROOM TEMPERATURE.

DO NOT TAKE BY MOUTH OR USE IN EYES.

COMPLETE PRESCRIBING INFORMATION IS ENCLOSED.

THIS BOX CONTAINS ONE APPLICATOR.